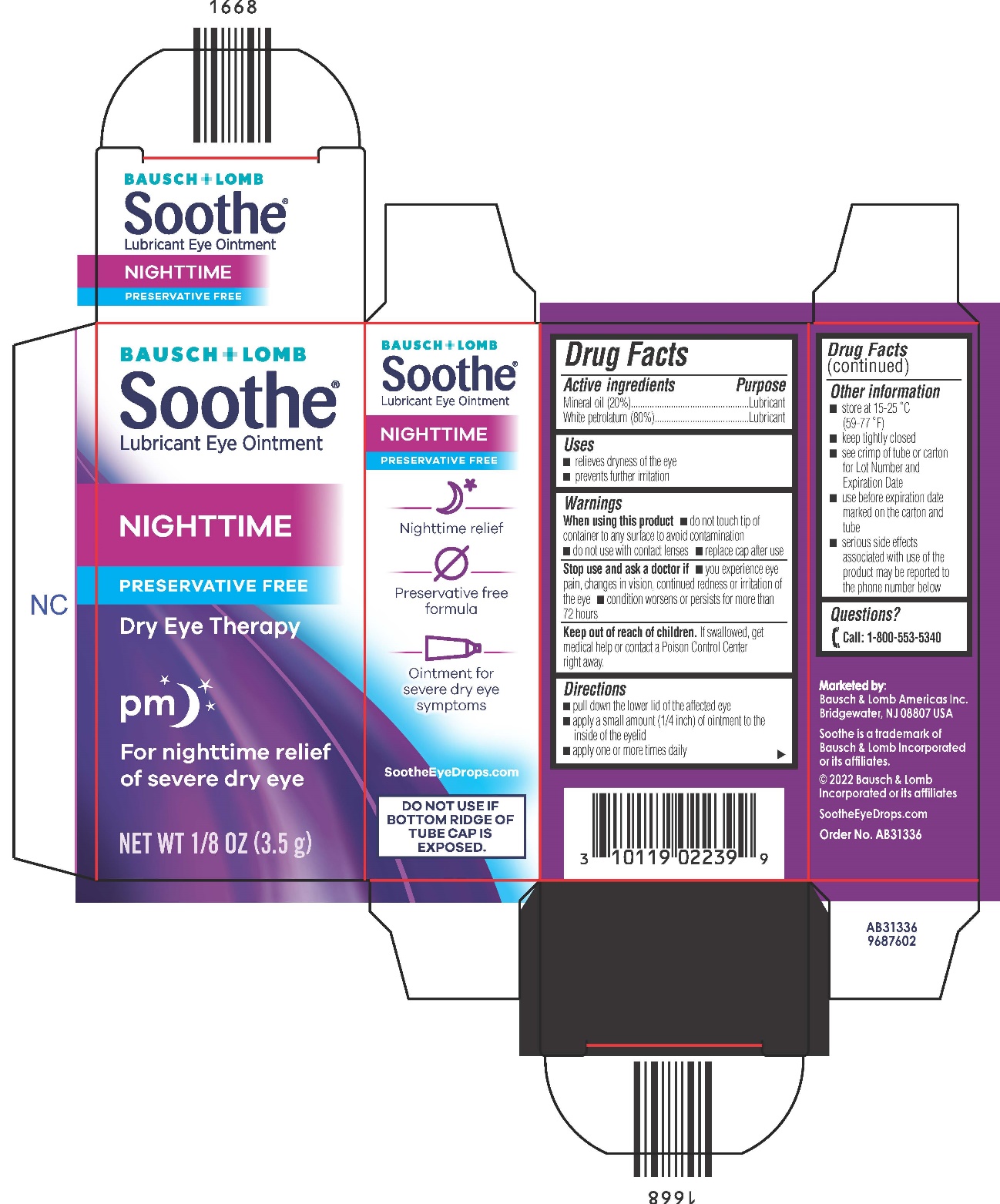 DRUG LABEL: Soothe Night Time
NDC: 24208-313 | Form: OINTMENT
Manufacturer: Bausch & Lomb Incorporated
Category: otc | Type: HUMAN OTC DRUG LABEL
Date: 20240924

ACTIVE INGREDIENTS: MINERAL OIL 200 mg/1 g; PETROLATUM 800 mg/1 g

Drug Facts

Active ingredients

Mineral oil (20%)
White petrolatum (80%)

Purpose

Lubricant
Lubricant

Uses

- relieves dryness of the eye
- prevents further irritation

Warnings

When using this product

- do not touch tip of container to any surface to avoid contamination
- do not use with contact lenses
- replace cap after use

Stop use and ask a doctor if

- you experience eye pain, changes in vision, continued redness or irritation of the eye
- condition worsens or persists for more than 72 hours

Keep out of reach of children.

If swallowed, get medical help or contact a Poison Control Center right away.

Directions

- pull down the lower lid of the affected eye
- apply a small amount (1/4 inch) of ointment to the inside of the eyelid
- apply one or more times daily

Inactive Ingredients

none.

Other information

- store at 15-25 °C (59-77 °F)
- keep tightly closed
- see crimp of tube or carton for Lot Number and Expiration Date
- use before expiration date marked on the carton and tube
- serious side effects associated with use of the product may be reported to the phone number below

Questions?

[phone icon] Call: 1-800-553-5340

Marketed by:
Bausch & Lomb Americas Inc.
Bridgewater, NJ 08807 USA

Soothe is a trademark of|
Bausch & Lomb Incorporated
or its affiliates.

© 2022 Bausch & Lomb
Incorporated or its affiliates

SootheEyeDrops.com

Order No. AB31336

Package/Label Principal Display Panel

BAUSCH + LOMB

Soothe®
Lubricant Eye Ointment

NIGHTTIME

PRSERVATIVE FREE

Dry Eye Therapy

pm[with moon and stars icon]

For nighttime relief
of severe dry eye

NET WT 1/8 OZ (3.5 g)

AB31336
96687602